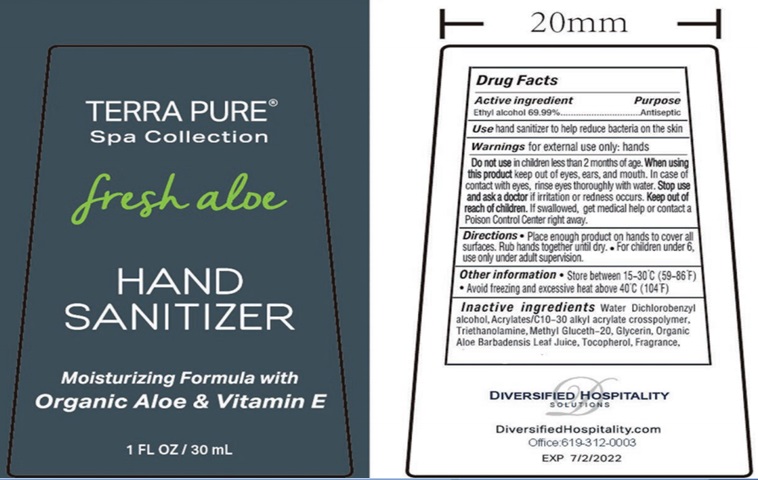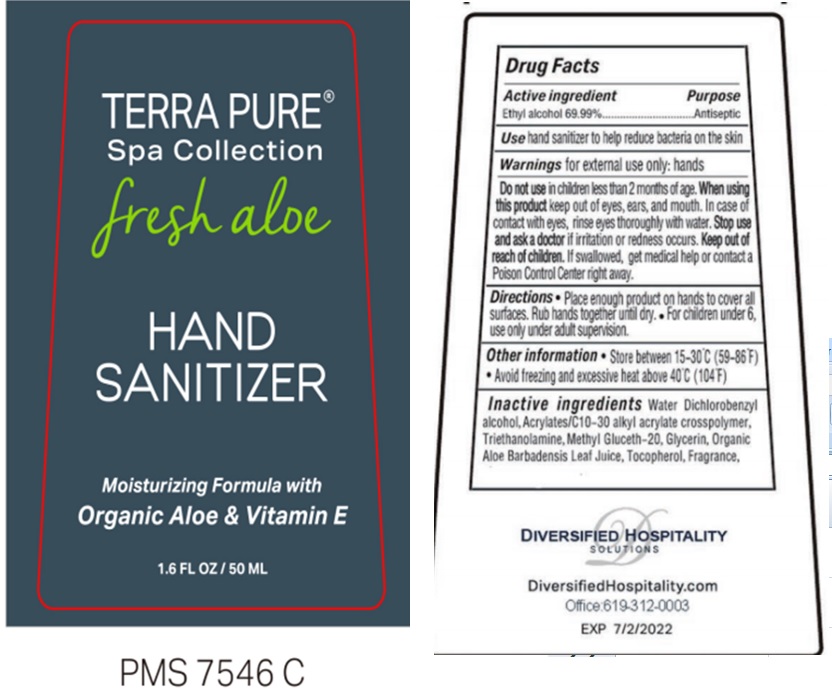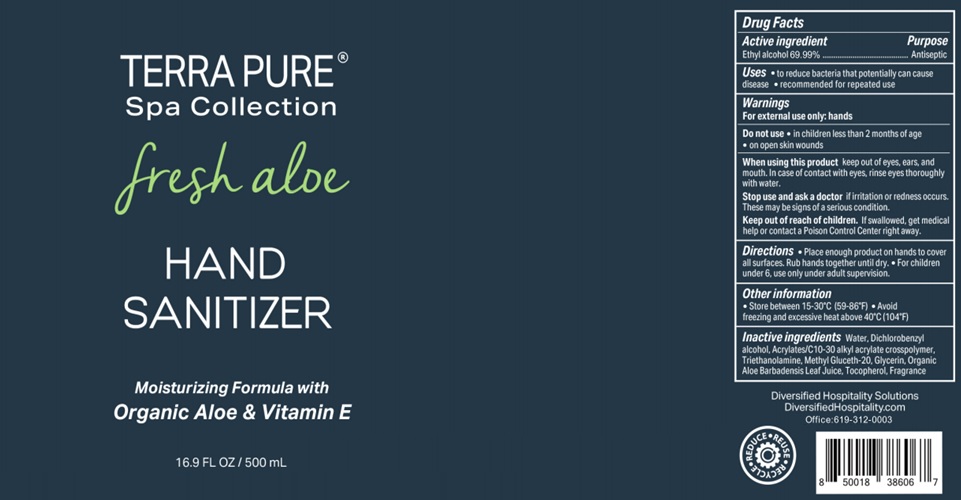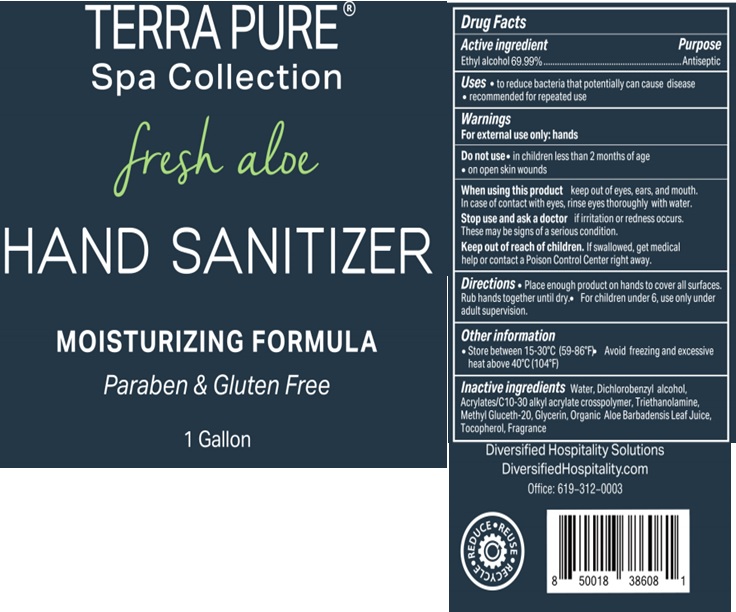 DRUG LABEL: Terra Pure Spa Collection Fresh Aloe Hand Sanitizer
NDC: 77849-007 | Form: GEL
Manufacturer: Yangzhou Eco-Amenities CO., Ltd
Category: otc | Type: HUMAN OTC DRUG LABEL
Date: 20200814

ACTIVE INGREDIENTS: ALCOHOL 0.6999 mL/1 mL
INACTIVE INGREDIENTS: WATER; DICHLOROBENZYL ALCOHOL; CARBOMER INTERPOLYMER TYPE A (ALLYL SUCROSE CROSSLINKED); TROLAMINE; METHYL GLUCETH-20; GLYCERIN; ALOE VERA LEAF; TOCOPHEROL

Terra Pure Spa Collection Fresh Aloe Hand Sanitizer

Active ingredient

Ethyl Alcohol 69.99% v/v

Purpose

Antiseptic

Use

hand sanitizer to help reduce bacteria on the skin

Warnings

for external use only: hands

Do not use

in children less than 2 months of age:

When using this product

keep out of eyes, ears, and mouth. In case of contact with eyes, rinse eyes thoroughly with water.

Stop use and ask a doctor

if irritation or redness occurs.

Keep out of reach of children.

If swallowed, get medical help or contact a Poison Control Center right away.

Directions

- Place enough product on hands to cover all surfaces. Rub hands together until dry.
- For children under 6, use only under adult supervision.

Other information

- Store between 15-30°C (59-86°F)
- Avoid freezing and excessive heat above 40°C (140°F)

Inactive Ingredients

Water, Dichlorobenzyl alcohol, Acrylates/C10-30 alkyl acrylate crosspolymer, Triethanolamine, Methyl Gluceth-20, Glycerin, Organic Aloe Barbadensis Leaf Juice, Tocopherol, Fragrance